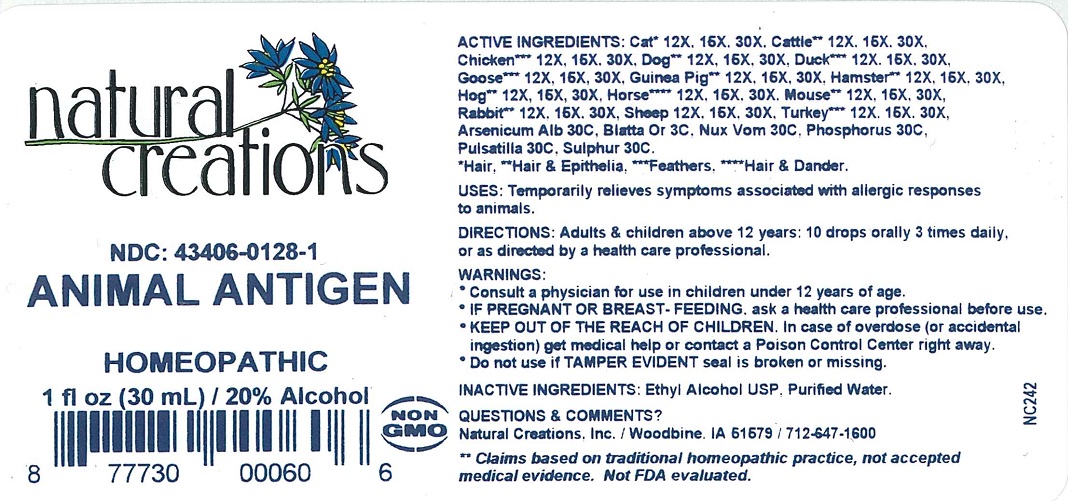 DRUG LABEL: ANIMAL ANTIGEN
NDC: 43406-0128 | Form: LIQUID
Manufacturer: Natural Creations, Inc.
Category: homeopathic | Type: HUMAN PRESCRIPTION DRUG LABEL
Date: 20220217

ACTIVE INGREDIENTS: FELIS CATUS HAIR 30 [hp_X]/1 mL; BOS TAURUS HAIR 30 [hp_X]/1 mL; BOS TAURUS SKIN 30 [hp_X]/1 mL; GALLUS GALLUS FEATHER 30 [hp_X]/1 mL; CANIS LUPUS FAMILIARIS HAIR 30 [hp_X]/1 mL; CANIS LUPUS FAMILIARIS SKIN 30 [hp_X]/1 mL; ANAS PLATYRHYNCHOS FEATHER 30 [hp_X]/1 mL; ANSER ANSER FEATHER 30 [hp_X]/1 mL; CAVIA PORCELLUS HAIR 30 [hp_X]/1 mL; CAVIA PORCELLUS SKIN 30 [hp_X]/1 mL; MESOCRICETUS AURATUS HAIR 30 [hp_X]/1 mL; MESOCRICETUS AURATUS SKIN 30 [hp_X]/1 mL; SUS SCROFA SKIN 30 [hp_X]/1 mL; SUS SCROFA HAIR 30 [hp_X]/1 mL; EQUUS CABALLUS HAIR 30 [hp_X]/1 mL; EQUUS CABALLUS DANDER 30 [hp_X]/1 mL; MUS MUSCULUS HAIR 30 [hp_X]/1 mL; MUS MUSCULUS SKIN 30 [hp_X]/1 mL; ORYCTOLAGUS CUNICULUS HAIR 30 [hp_X]/1 mL; ORYCTOLAGUS CUNICULUS SKIN 30 [hp_X]/1 mL; OVIS ARIES WHOLE 30 [hp_X]/1 mL; MELEAGRIS GALLOPAVO FEATHER 30 [hp_X]/1 mL; ARSENIC TRIOXIDE 30 [hp_C]/1 mL; BLATTA ORIENTALIS 30 [hp_C]/1 mL; STRYCHNOS NUX-VOMICA SEED 30 [hp_C]/1 mL; PHOSPHORUS 30 [hp_C]/1 mL; ANEMONE PULSATILLA 30 [hp_C]/1 mL; SULFUR 30 [hp_C]/1 mL
INACTIVE INGREDIENTS: WATER; ALCOHOL

ANIMAL ANTIGEN

ACTIVE INGREDIENT

ACTIVE INGREDIENTS: Cat* 12X, 15X, 30X, Cattle** 12X, 15X, 30X, Chicken*** 12X, 15X, 30X, Dog** 12X, 15X, 30X, Duck*** 12X, 15X, 30X, Goose*** 12X, 15X, 30X, Guinea Pig** 12X, 15X, 30X, Hamster** 12X, 15X, 30X, Hog**12X, 15X, 30X, Horse**** 12X, 15X, 30X, Mouse** 12X, 15X, 30X, Rabbit** 12X, 15X, 30X, Sheep 12X, 15X, 30X, Turkey*** 12X, 15X, 30X, Arsenicum Album 30C, Blata Orientalis 30C, Nux Vomica 30C, Phosphorus 30C, Pulsatilla 30C, Sulphur 30C.

*Hair, **Hair & Epithelia, ***Feathers, ****Hair & Dander.

PURPOSE

Uses: Temporarily relieves symptoms associated with allergic responses to animals.**

INDICATIONS AND USAGE

Uses: Temporarily relieves symptoms associated with allergic responses to animals.

DOSAGE AND ADMINISTRATION

Directions: Adults & children above 12 years: 10 drops orally 3 times daily, or as directed by a health care professional.

WARNINGS:

- Consult a physician for use in children under 12 years of age.

- IF PREGNANT OR BREAST-FEEDING, ask a health care professional before use.
- KEEP OUT OF THE REACH OF CHILDREN. In case of overdose (or accidental ingestion) get medical help or contact a Poison Control Center right away.
- Do not use if TAMPER EVIDENT seal is broken or missing.

WARNINGS:

- Consult a physician for use in children under 12 years of age.

- IF PREGNANT OR BREAST-FEEDING, ask a health care professional before use.
- KEEP OUT OF THE REACH OF CHILDREN. In case of overdose (or accidental ingestion) get medical help or contact a Poison Control Center right away.
- Do not use if TAMPER EVIDENT seal is broken or missing.

Inactive Ingredients: Purified Water, Ethyl Alcohol USP.

Questions & Comments?

Natural Creations, Inc. / Woodbine, IA 51579 / 712-647-1600

REFERENCES

**Claims based on traditional homeopathic practice, not accepted medical evidence. Not FDA evaluated.

PACKAGE LABEL

NDC: 43406-0128-1

ANIMAL ANTIGEN

HOMEOPATHIC

1 fl oz (30 mL) / 20% Alcohol

UPC: 877730000606 NON GMO Logo